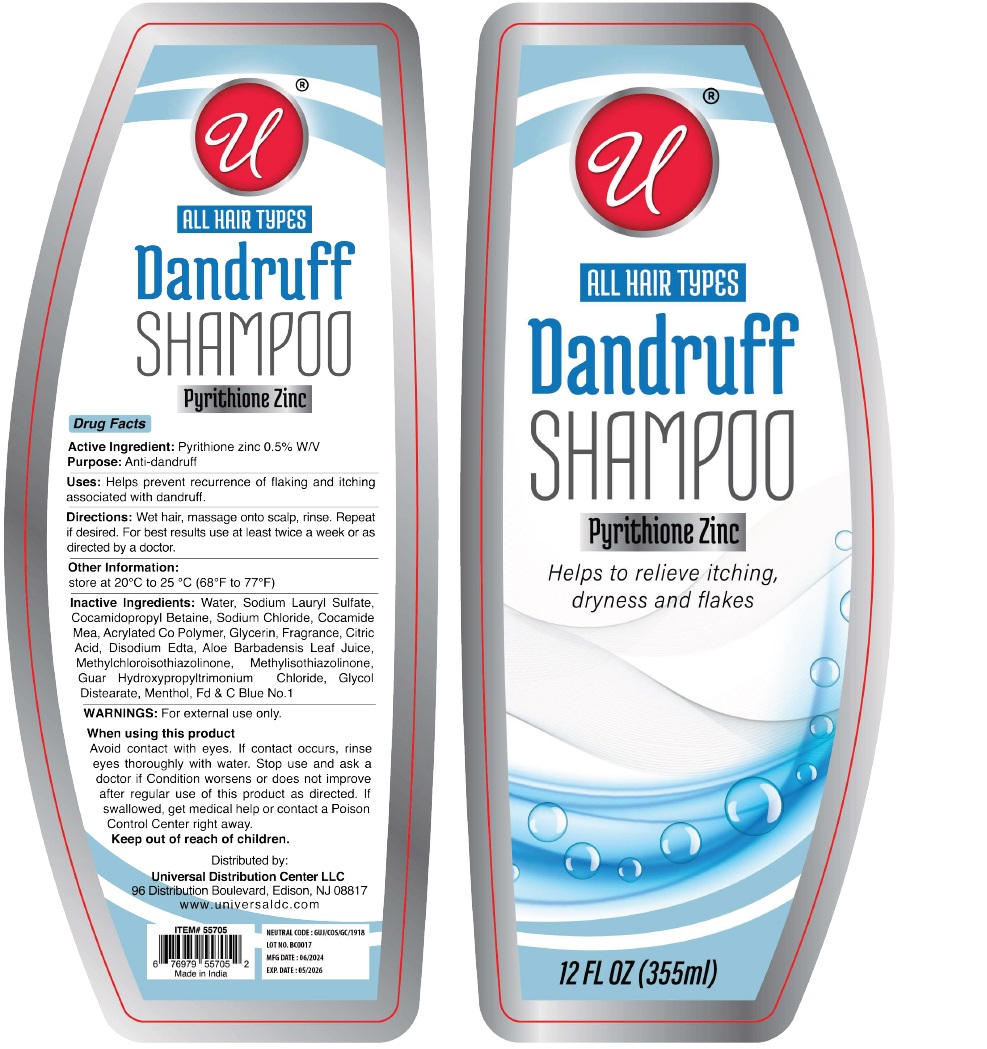 DRUG LABEL: Pyrithione Zinc 0.5 Dandruff
NDC: 52000-416 | Form: SHAMPOO
Manufacturer: Universal Distribution Center LLC
Category: otc | Type: HUMAN OTC DRUG LABEL
Date: 20240429

ACTIVE INGREDIENTS: PYRITHIONE ZINC 0.5 g/100 mL
INACTIVE INGREDIENTS: WATER; SODIUM LAURYL SULFATE; COCAMIDOPROPYL BETAINE; SODIUM CHLORIDE; COCO MONOETHANOLAMIDE; BUTYL ACRYLATE/METHYL METHACRYLATE/METHACRYLIC ACID COPOLYMER (18000 MW); GLYCERIN; CITRIC ACID MONOHYDRATE; EDETATE DISODIUM; ALOE VERA LEAF; METHYLCHLOROISOTHIAZOLINONE; METHYLISOTHIAZOLINONE; GUAR HYDROXYPROPYLTRIMONIUM CHLORIDE; GLYCOL DISTEARATE; MENTHOL, UNSPECIFIED FORM; FD&C BLUE NO. 1

Dandruff SHAMPOO ALL HAIR TYPES

Active Ingredient:

Pyrithione zinc 0.5% W/V

Purpose:

Anti-dandruff

Uses:

Helps prevent recurrence of flaking and itching associated with dandruff.

Directions:

Wet hair, massage onto scalp, rinse. Repeat if desired. For best results use at least twice a week or as directed by a doctor.

Other Information:

Store at 20°C to 25°C (68°F to 77°F)

Inactive Ingredients:

Water, Sodium Lauryl Sulfate, Cocamidopropyl Betaine, Sodium Chloride, Cocamide Mea, Acrylated Co Polymer, Glycerin, Fragrance, Citric Acid, Disodium Edta, Aloe Barbadensis Leaf Juice, Methylchloroisothiazolinone, Methylisothiazolinone, Guar Hydroxypropyltrimonium Chloride, Glycol Distearate, Menthol, Fd & C Blue No.1

WARNINGS:

For external use only.

When using this product
Avoid contact with eyes. If contact occurs, rinse eyes thoroughly with water. Stop use and ask a doctor if Condition worsens or does not improve after regular use of this product as directed. If swallowed, get medical help or contact a Poison Control Center right away.

Keep out of reach of children.

ALL HAIR TYPES

Helps to relieve itching, dryness and flakes

Distributed by:
Universal Distribution Center LLC
96 Distribution Boulevard, Edison, NJ 08817
www.universaldc.com

Made in India